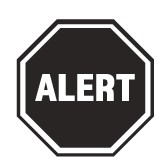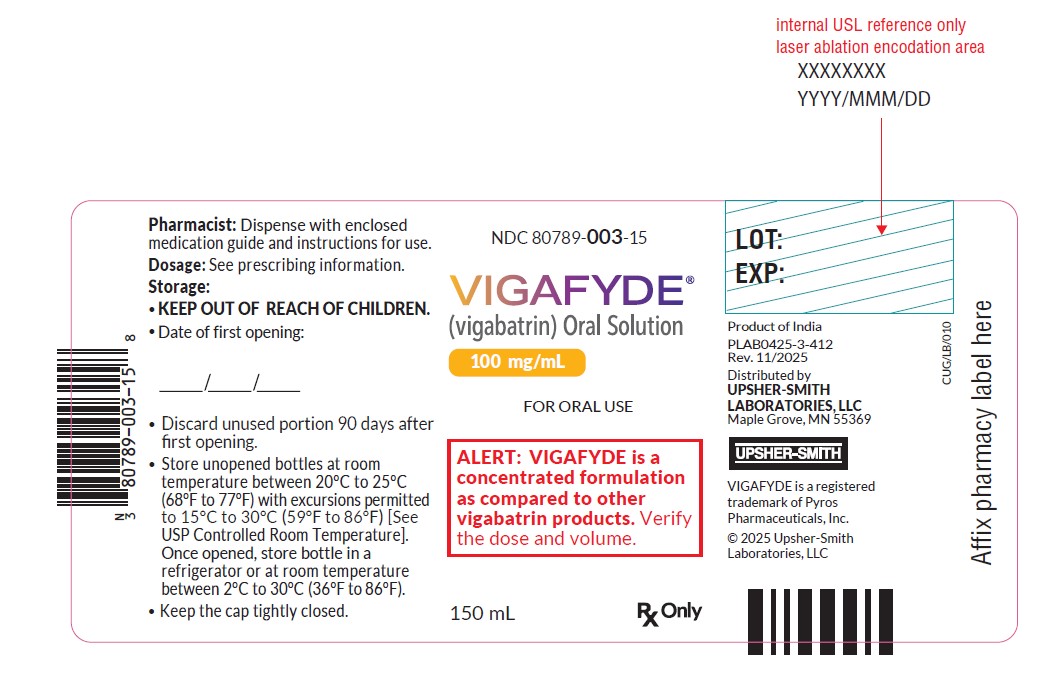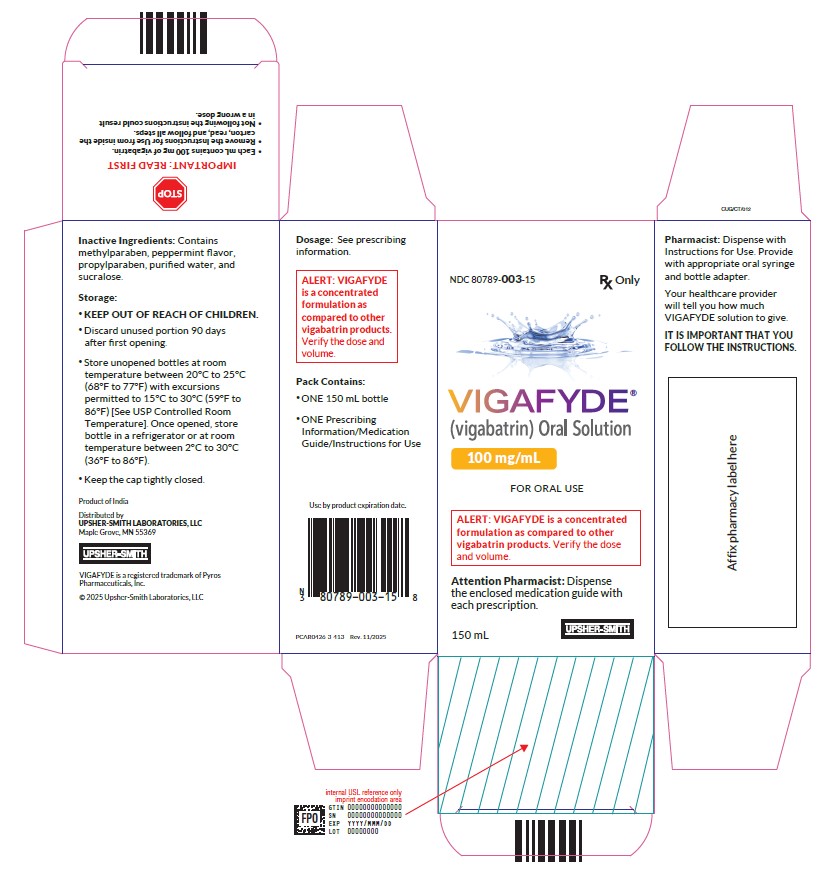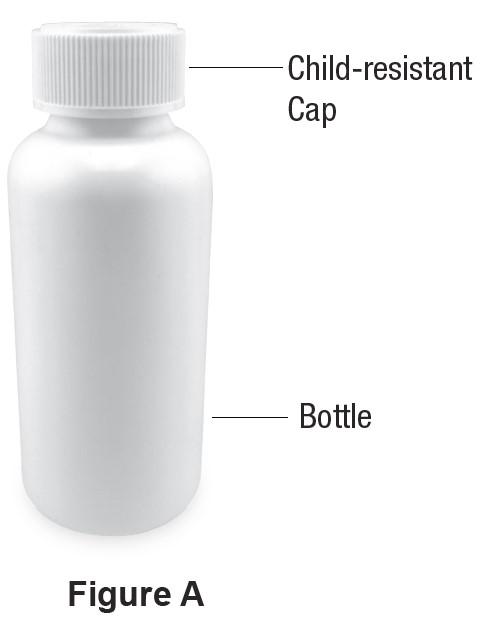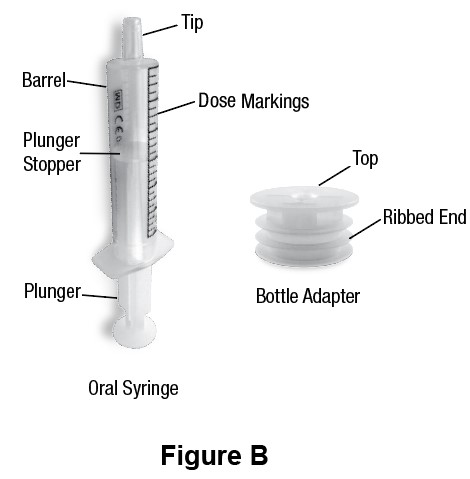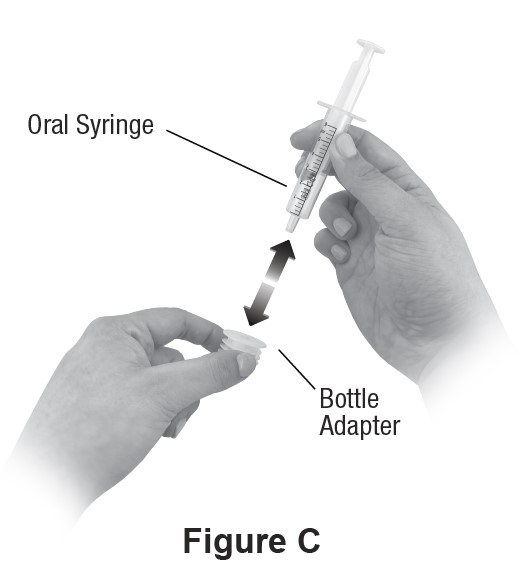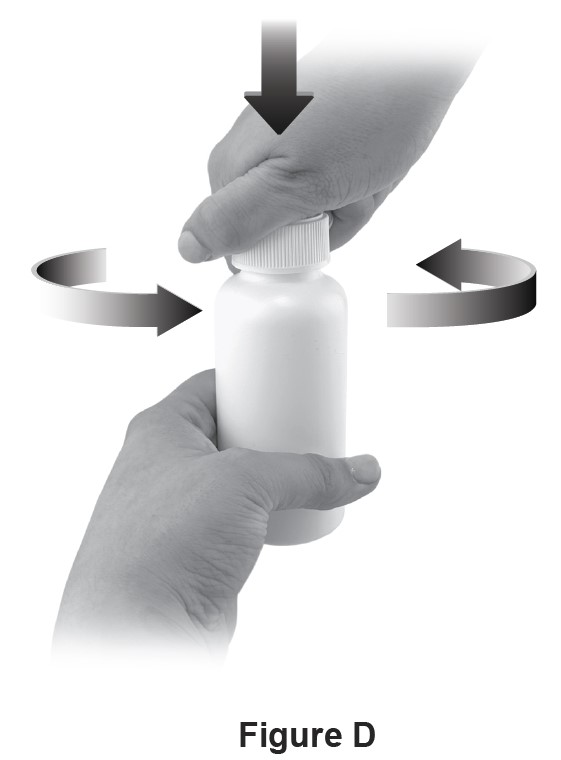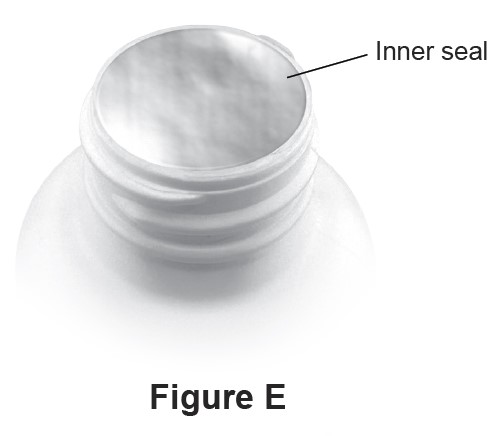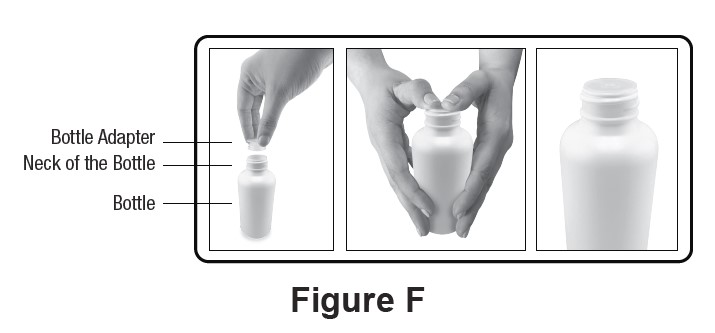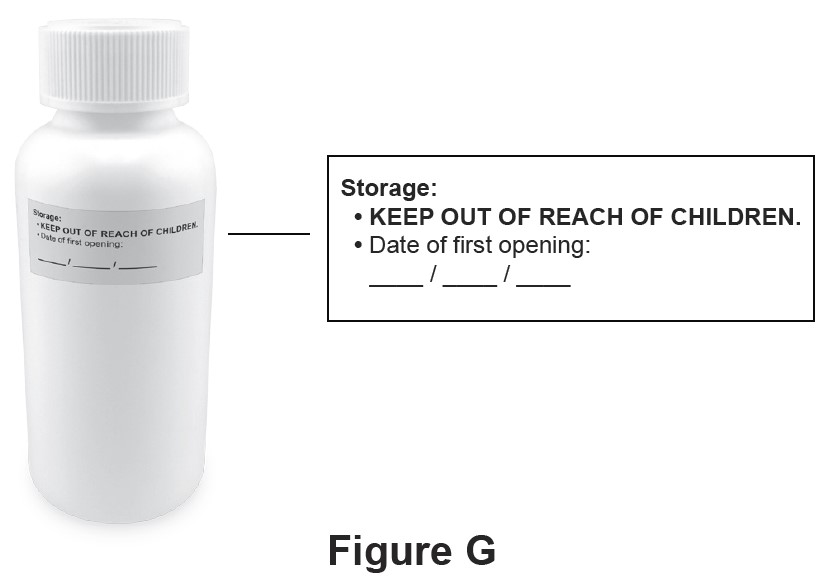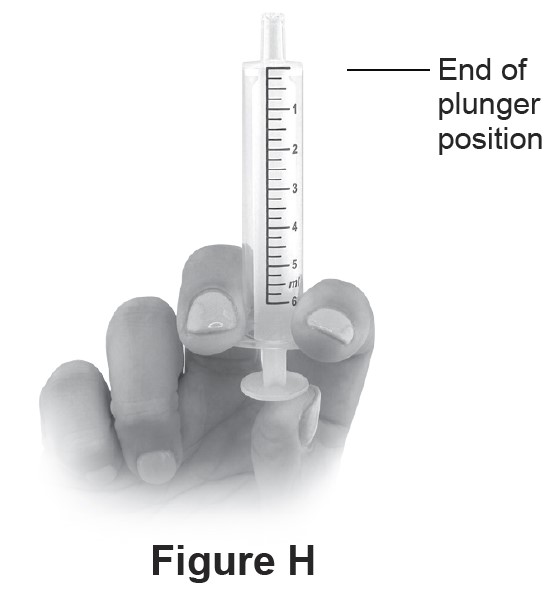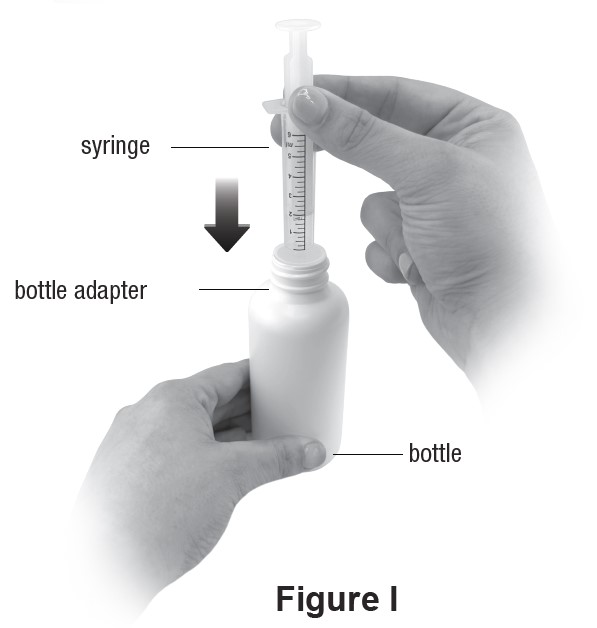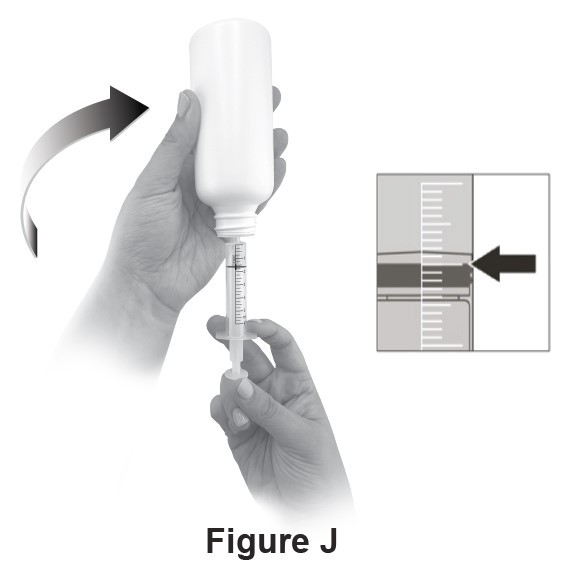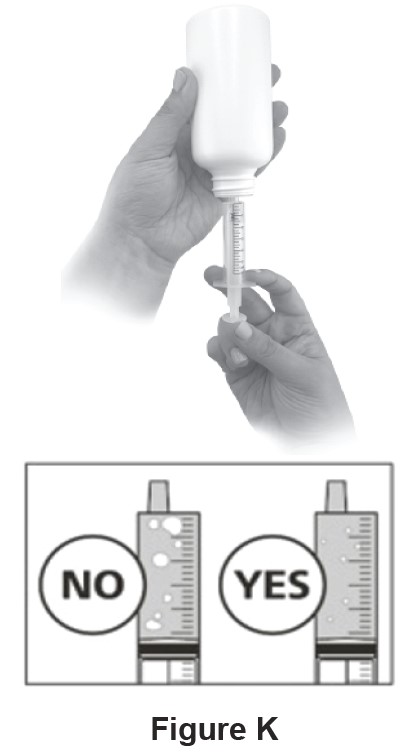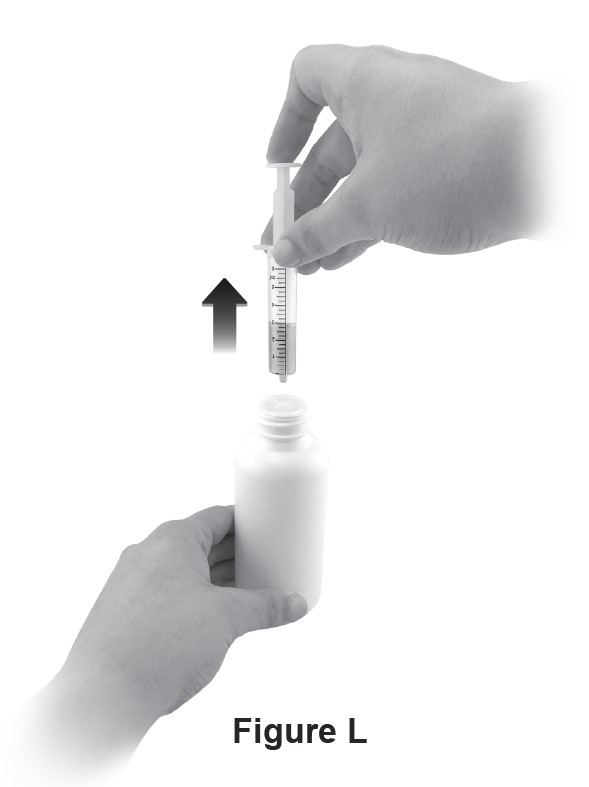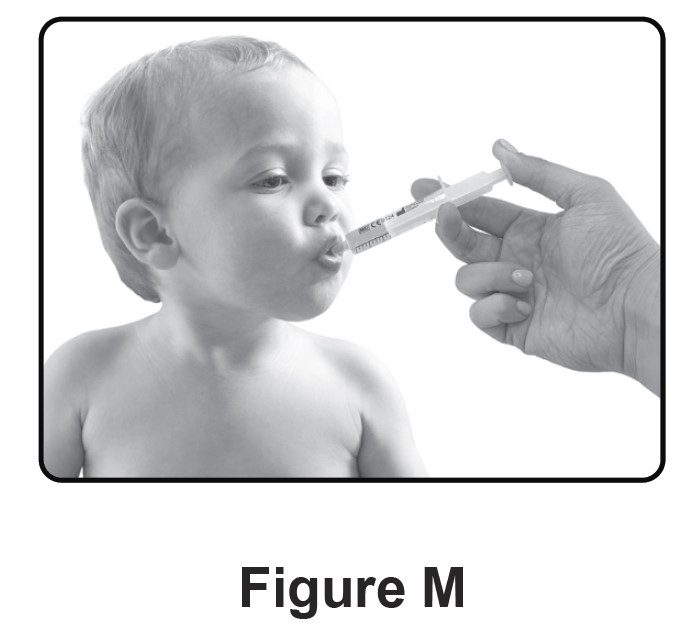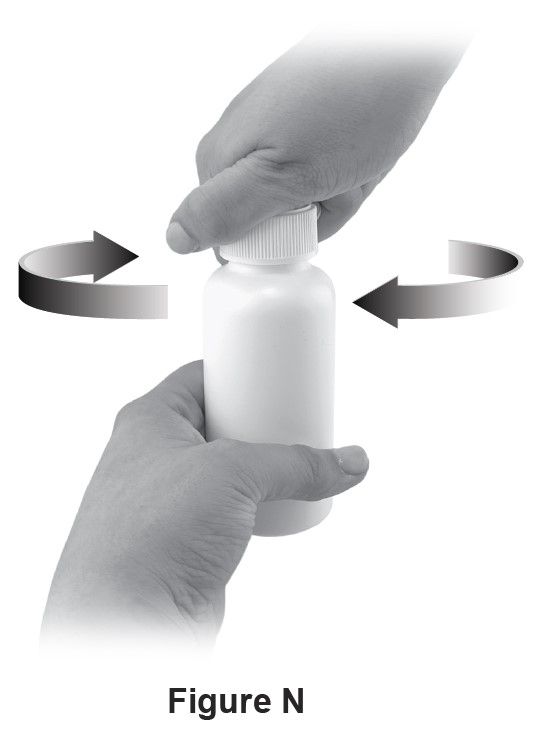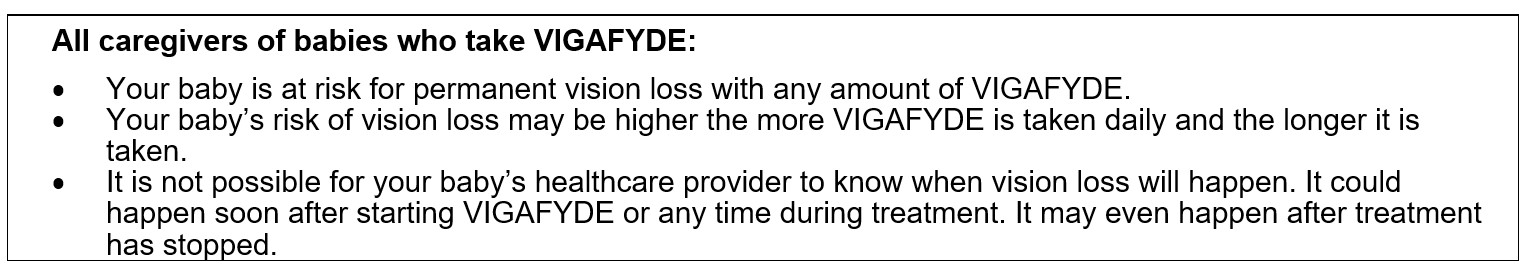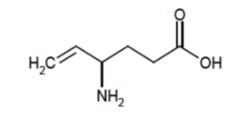 DRUG LABEL: VIGAFYDE
NDC: 80789-003 | Form: SOLUTION
Manufacturer: Upsher-Smith Laboratories, LLC
Category: prescription | Type: HUMAN PRESCRIPTION DRUG LABEL
Date: 20251101

ACTIVE INGREDIENTS: VIGABATRIN 100 mg/1 mL

HIGHLIGHTS OF PRESCRIBING INFORMATION

These highlights do not include all the information needed to use VIGAFYDE safely and effectively. See full prescribing information for VIGAFYDE.
VIGAFYDE® (vigabatrin) oral solution
Initial U.S. Approval: 2009

WARNING: PERMANENT VISION LOSS

See full prescribing information for complete boxed warning.

- VIGAFYDE can cause permanent bilateral concentric visual field constriction, including tunnel vision that can result in disability. In some cases, VIGAFYDE may also decrease visual acuity. (5.1)
- Risk increases with increasing dose and cumulative exposure, but there is no dose or exposure to VIGAFYDE known to be free of risk of vision loss. (5.1)
- Risk of new and worsening vision loss continues as long as VIGAFYDE is used, and possibly after discontinuing VIGAFYDE. (5.1)
- Baseline and periodic vision assessment is recommended for patients on VIGAFYDE. However, this assessment cannot always prevent vision damage. (5.1)
- VIGAFYDE is available only through a restricted program called the Vigabatrin REMS. (5.2)

RECENT MAJOR CHANGES

Dosage and Administration (2.1) 9/2025

Warnings and Precautions (5.2) 9/2025

1 INDICATIONS AND USAGE

VIGAFYDE is indicated as monotherapy for the treatment of infantile spasms in pediatric patients 1 month to 2 years of age for whom the potential benefits outweigh the potential risk of vision loss. (1)

2 DOSAGE AND ADMINISTRATION

- VIGAFYDE is a concentrated formulation as compared to other vigabatrin products. Verify the strength and the dose of the product prior to prescribing, dispensing, and administering. (2.1)
- Administer VIGAFYDE orally or via gastrostomy (G) tube. Doses administered via gastrojejunal (GJ) tubes must be administered through the G-port. (2.1)
- Initiate at a daily dosage of 50 mg/kg (25 mg/kg twice daily); increase total daily dosage every 3 days, in increments of 25 mg/kg/day to 50 mg/kg/day, up to a maximum daily dosage of 150 mg/kg (75 mg/kg twice daily). (2.2)

3 DOSAGE FORMS AND STRENGTHS

- Oral Solution : 100 mg/mL (3)

4 CONTRAINDICATIONS

None (4)

5 WARNINGS AND PRECAUTIONS

- Abnormal MRI signal changes and intramyelinic edema have been reported in some infants with infantile spasms receiving VIGAFYDE. (5.3, 5.4)
- Withdrawal of AEDs: Taper dose to avoid withdrawal seizures. (5.5)
- Anemia: Monitor for symptoms of anemia. (5.6)

6 ADVERSE REACTIONS

The most common adverse reactions (incidence ˃5% and greater than on placebo) in patients with infantile spasms include somnolence, bronchitis, ear infection, and acute otitis media. (6.1)

To report SUSPECTED ADVERSE REACTIONS, contact Upsher-Smith Laboratories, LLC at 1-855-899-9180 or FDA at 1-800-FDA-1088 or www.fda.gov/medwatch.

7 DRUG INTERACTIONS

Decreased phenytoin plasma levels: Dosage adjustment may be needed. (7.1)

FULL PRESCRIBING INFORMATION

WARNING: PERMANENT VISION LOSS

- VIGAFYDE can cause permanent bilateral concentric visual field constriction, including tunnel vision that can result in disability. In some cases, VIGAFYDE also can damage the central retina and may decrease visual acuity [see Warnings and Precautions (5.1)].
- The onset of vision loss from VIGAFYDE is unpredictable, and can occur within weeks of starting treatment or sooner, or at any time after starting treatment, even after months or years.
- Symptoms of vision loss from VIGAFYDE are unlikely to be recognized by patients or caregivers before vision loss is severe. Vision loss of milder severity, while often unrecognized by the patient or caregiver, can still adversely affect function.
- The risk of vision loss increases with increasing dose and cumulative exposure, but there is no dose or exposure known to be free of risk of vision loss.
- Vision assessment is recommended at baseline (no later than 4 weeks after starting VIGAFYDE), at least every 3 months during therapy, and about 3 to 6 months after the discontinuation of therapy.
- Once detected, vision loss due to VIGAFYDE is not reversible. It is expected that, even with frequent monitoring, some patients will develop severe vision loss.
- Consider drug discontinuation, balancing benefit and risk, if vision loss is documented.
- Risk of new or worsening vision loss continues as long as VIGAFYDE is used. It is possible that vision loss can worsen despite discontinuation of VIGAFYDE.
- Because of the risk of vision loss, VIGAFYDE should be withdrawn from patients with infantile spasms who fail to show substantial clinical benefit within 2 to 4 weeks of initiation, or sooner if treatment failure becomes obvious. Patient response to and continued need for VIGAFYDE should be periodically reassessed.
- VIGAFYDE should not be used in patients with, or at high risk of, other types of irreversible vision loss unless the benefits of treatment clearly outweigh the risks.
- VIGAFYDE should not be used with other drugs associated with serious adverse ophthalmic effects such as retinopathy or glaucoma unless the benefits clearly outweigh the risks.
- Use the lowest dosage and shortest exposure to VIGAFYDE consistent with clinical objectives [see Dosage and Administration (2.1)].

Because of the risk of permanent vision loss, VIGAFYDE is available only through a restricted program under a Risk Evaluation and Mitigation Strategy (REMS) called the Vigabatrin REMS [see Warnings and Precautions (5.1)]. Further information is available at www.vigabatrinREMS.com or call 1-866-244-8175.

1 INDICATIONS AND USAGE

VIGAFYDE is indicated as monotherapy for the treatment of infantile spasms in pediatric patients 1 month to 2 years of age for whom the potential benefits outweigh the potential risk of vision loss [see Warnings and Precautions (5.1)].

2 DOSAGE AND ADMINISTRATION

2.1 Important Dosing and Administration Instructions

Dosing

VIGAFYDE is a solution of 100 mg/mL of vigabatrin. VIGAFYDE is a concentrated solution as compared to other vigabatrin products. Verify strength and the dose of the product prior to prescribing, dispensing, and administering [see Dosage and Administration (2.3)]. VIGAFYDE does not require additional reconstitution or dilution prior to administration.

Use the lowest dosage and shortest exposure to VIGAFYDE consistent with clinical objectives [see Warnings and Precautions (5.1)].

The VIGAFYDE dosing regimen depends on weight.

Monitoring of VIGAFYDE plasma concentrations to optimize therapy is not helpful.

Administration

Administer VIGAFYDE orally or via gastrostomy (G) tube. Doses administered via gastrojejunal (GJ) tubes must be administered through the G-port. After G-tube administration, flush with water.

VIGAFYDE can be given with or without food.

A calibrated measuring device is recommended to measure and deliver the prescribed dose accurately. A household teaspoon or tablespoon is not an adequate measuring device.

If a decision is made to discontinue VIGAFYDE, the dose should be gradually reduced [see Dosage and Administration (2.4) and Warnings and Precautions (5.5)].

2.2 Recommended Dosage for Infantile Spasms

The initial daily dosing is 50 mg/kg/day given in two divided doses (25 mg/kg twice daily); subsequent dosing can be titrated by 25 mg/kg/day to 50 mg/kg/day increments every 3 days, up to a maximum of 150 mg/kg/day given in 2 divided doses (75 mg/kg twice daily) [see Use in Specific Populations (8.4)].

Table 1 provides the volume of the 100 mg/mL dosing solution that should be administered as individual doses in infants of various weights.

Table 1. Dosing of VIGAFYDE for Infantile Spasms
Weight [kg] | Starting Dose 50 mg/kg/day | Maximum Dose 150 mg/kg/day
3 | 75 mg (0.75 mL) twice daily | 225 mg (2.25 mL) twice daily
4 | 100 mg (1 mL) twice daily | 300 mg (3 mL) twice daily
5 | 125 mg (1.25 mL) twice daily | 375 mg (3.75 mL) twice daily
6 | 150 mg (1.5 mL) twice daily | 450 mg (4.5 mL) twice daily
7 | 175 mg (1.75 mL) twice daily | 525 mg (5.25 mL) twice daily
8 | 200 mg (2 mL) twice daily | 600 mg (6 mL) twice daily
9 | 225 mg (2.25 mL) twice daily | 675 mg (6.75 mL) twice daily
10 | 250 mg (2.5 mL) twice daily | 750 mg (7.5 mL) twice daily
11 | 275 mg (2.75 mL) twice daily | 825 mg (8.25 mL) twice daily
12 | 300 mg (3 mL) twice daily | 900 mg (9 mL) twice daily
13 | 325 mg (3.25 mL) twice daily | 975 mg (9.75 mL) twice daily
14 | 350 mg (3.5 mL) twice daily | 1,050 mg (10.5 mL) twice daily
15 | 375 mg (3.75 mL) twice daily | 1,125 mg (11.25 mL) twice daily
16 | 400 mg (4 mL) twice daily | 1,200 mg (12 mL) twice daily

In patients with infantile spasms, VIGAFYDE should be withdrawn if a substantial clinical benefit is not observed within 2 to 4 weeks. If, in the clinical judgment of the prescriber, evidence of treatment failure becomes obvious earlier than 2 to 4 weeks, treatment should be discontinued at that time [see Warnings and Precautions (5.1)].

2.3 Switching Between Other Vigabatrin Products and VIGAFYDE

If switching between other vigabatrin products and VIGAFYDE, ensure the correct volume for the correct dosage is prescribed, dispensed, and administered. As compared to other vigabatrin products, VIGAFYDE is a concentrated solution that requires a smaller volume than other vigabatrin products to obtain the same dosage (i.e., VIGAFYDE is 100 mg/mL and currently available vigabatrin for oral solution products have a final concentration of 50 mg/mL).

2.4 Discontinuation of VIGAFYDE

Avoid abrupt withdrawal [see Warnings and Precautions (5.5)]. In a controlled clinical study in patients with infantile spasms, vigabatrin was tapered by decreasing the daily dosage at a rate of 25 to 50 mg/kg every 3 to 4 days.

3 DOSAGE FORMS AND STRENGTHS

Oral Solution : 100 mg/mL clear, colorless to light yellow solution with a peppermint odor.

4 CONTRAINDICATIONS

None.

5 WARNINGS AND PRECAUTIONS

5.1 Permanent Vision Loss

VIGAFYDE can cause permanent vision loss. Because of this risk and because, when it is effective, VIGAFYDE provides an observable symptomatic benefit; patient response and continued need for treatment should be periodically assessed.

VIGAFYDE is indicated for treatment in patients 1 month to 2 years of age [see Indications and Usage (1)]. VIGAFYDE is not approved for use in pediatric patients older than 2 years of age or in adults. Based upon adult studies, 30 percent or more of patients can be affected with bilateral concentric visual field constriction ranging in severity from mild to severe. Severe cases may be characterized by tunnel vision to within 10 degrees of visual fixation, which can result in disability. In some cases, VIGAFYDE also can damage the central retina and may decrease visual acuity. Symptoms of vision loss from VIGAFYDE are unlikely to be recognized by patients or caregivers before vision loss is severe. Vision loss of milder severity, while often unrecognized by the patient or caregiver, can still adversely affect function.

Because assessing vision may be difficult in infants and children, the frequency and extent of vision loss is poorly characterized in these patients. For this reason, the understanding of the risk is primarily based on the adult experience. The possibility that vision loss from VIGAFYDE may be more common, more severe, or have more severe functional consequences in infants than in adults cannot be excluded.

The onset of vision loss from VIGAFYDE is unpredictable and can occur within weeks of starting treatment or sooner, or at any time after starting treatment, even after months or years.

The risk of vision loss increases with increasing dose and cumulative exposure, but there is no dose or exposure known to be free of risk of vision loss.

In patients with infantile spasms, VIGAFYDE should be withdrawn if a substantial clinical benefit is not observed within 2 to 4 weeks. If, in the clinical judgment of the prescriber, evidence of treatment failure becomes obvious earlier than 2 to 4 weeks, treatment should be discontinued at that time [see Dosage and Administration (2.2) and Warnings and Precautions (5.5)].

VIGAFYDE should not be used in patients with, or at high risk of, other types of irreversible vision loss unless the benefits of treatment clearly outweigh the risks. The interaction of other types of irreversible vision damage with vision damage from VIGAFYDE has not been well-characterized, but is likely adverse.

VIGAFYDE should not be used with other drugs associated with serious adverse ophthalmic effects such as retinopathy or glaucoma unless the benefits clearly outweigh the risks.

Monitoring of Vision

Monitoring of vision by an ophthalmic professional with expertise in visual field interpretation and the ability to perform dilated indirect ophthalmoscopy of the retina is recommended [see Warnings and Precautions (5.2)]. Because vision testing in infants is difficult, vision loss may not be detected until it is severe. For patients receiving VIGAFYDE, vision assessment is recommended at baseline (no later than 4 weeks after starting VIGAFYDE), at least every 3 months while on therapy, and about 3 to 6 months after the discontinuation of therapy. The diagnostic approach should be individualized for the patient and clinical situation.

In cooperative pediatric patients, perimetry is recommended, preferably by automated threshold visual field testing. Additional testing may also include electrophysiology (e.g., electroretinography [ERG]), retinal imaging (e.g., optical coherence tomography [OCT]), and/or other methods appropriate for the patient. In patients who cannot be tested, treatment may continue according to clinical judgment, with appropriate caregiver counseling. Because of variability, results from ophthalmic monitoring must be interpreted with caution, and repeat assessment is recommended if results are abnormal or uninterpretable. Repeat assessment in the first few weeks of treatment is recommended to establish if, and to what degree, reproducible results can be obtained, and to guide selection of appropriate ongoing monitoring for the patient.

The onset and progression of vision loss from VIGAFYDE is unpredictable, and it may occur or worsen precipitously between assessments. Once detected, vision loss due to VIGAFYDE is not reversible. It is expected that even with frequent monitoring, some VIGAFYDE patients will develop severe vision loss. Consider drug discontinuation, balancing benefit and risk, if vision loss is documented. It is possible that vision loss can worsen despite discontinuation of VIGAFYDE.

5.2 Vigabatrin REMS

VIGAFYDE is available only through a restricted distribution program called the Vigabatrin REMS, because of the risk of permanent vision loss.

Notable requirements of the Vigabatrin REMS include the following:

- Prescribers must be certified by enrolling in the program, agreeing to counsel caregivers on the risk of vision loss and the need for periodic monitoring of vision, and reporting any event suggestive of vision loss to the REMS program.
- Patients must enroll in the program.
- Pharmacies must be certified and must only dispense to patients authorized to receive VIGAFYDE.

Further information is available at www.vigabatrinREMS.com or by calling 1-866-244-8175.

5.3 Magnetic Resonance Imaging Abnormalities in Infants

Abnormal magnetic resonance imaging (MRI) signal changes characterized by increased T2 signal and restricted diffusion in a symmetric pattern involving the thalamus, basal ganglia, brain stem, and cerebellum have been observed in some infants treated with vigabatrin.

In a retrospective epidemiologic study in infants with infantile spasms (N=205), the prevalence of MRI changes was 22% in vigabatrin-treated patients versus 4% in patients treated with other therapies. In this study, in postmarketing experience, and in published literature reports, these changes generally resolved with discontinuation of treatment. In a few patients, the lesion resolved despite continued use. It has been reported that some infants exhibited coincident motor abnormalities, but no causal relationship has been established and the potential for long-term clinical sequelae has not been adequately studied.

Neurotoxicity (brain histopathology and neurobehavioral abnormalities) was observed in rats exposed to vigabatrin during late gestation and the neonatal and juvenile periods of development, and brain histopathological changes were observed in dogs exposed to vigabatrin during the juvenile period of development. The relationship between these findings and the abnormal MRI findings in infants treated with vigabatrin for infantile spasms is unknown [see Warnings and Precautions (5.4) and Use in Specific Populations (8.1)].

5.4 Neurotoxicity

Intramyelinic Edema (IME) has been reported in postmortem examination of infants being treated for infantile spasms with vigabatrin.

Abnormal MRI signal changes characterized by increased T2 signal and restricted diffusion in a symmetric pattern involving the thalamus, basal ganglia, brain stem, and cerebellum have also been observed in some infants treated for IS with vigabatrin [see Warnings and Precautions (5.3)].

Vacuolation, characterized by fluid accumulation and separation of the outer layers of myelin, has been observed in brain white matter tracts in adult and juvenile rats and adult mice, dogs, and possibly monkeys following administration of vigabatrin. This lesion, referred to as intramyelinic edema (IME), was seen in animals at doses within the human therapeutic range. A no-effect dose was not established in rodents or dogs. In the rat and dog, vacuolation was reversible following discontinuation of vigabatrin treatment, but, in the rat, pathologic changes consisting of swollen or degenerating axons, mineralization, and gliosis were seen in brain areas in which vacuolation had been previously observed. Vacuolation in adult animals was correlated with alterations in MRI and changes in visual and somatosensory EP.

Administration of vigabatrin to rats during the neonatal and juvenile periods of development produced vacuolar changes in the brain gray matter (including the thalamus, midbrain, deep cerebellar nuclei, substantia nigra, hippocampus, and forebrain) which are considered distinct from the IME observed in vigabatrin-treated adult animals. Decreased myelination and evidence of oligodendrocyte injury were additional findings in the brains of vigabatrin-treated rats. An increase in apoptosis was seen in some brain regions following vigabatrin exposure during the early postnatal period. Long-term neurobehavioral abnormalities (convulsions, neuromotor impairment, learning deficits) were also observed following vigabatrin treatment of young rats. Administration of vigabatrin to juvenile dogs produced vacuolar changes in the brain gray matter (including the septal nuclei, hippocampus, hypothalamus, thalamus, cerebellum, and globus pallidus). Neurobehavioral effects of vigabatrin were not assessed in the juvenile dog. These effects in young animals occurred at doses lower than those producing neurotoxicity in adult animals and were associated with plasma vigabatrin levels substantially lower than those achieved clinically in infants [see Use in Specific Populations (8.4)].

In a published study, vigabatrin (200, 400 mg/kg/day) induced apoptotic neurodegeneration in the brain of young rats when administered by intraperitoneal injection on postnatal days 5 to 7.

5.5 Withdrawal of Antiepileptic Drugs

As with all antiepileptic drugs, VIGAFYDE should be withdrawn gradually [see Dosage and Administration (2.4)]. However, if withdrawal is needed because of a serious adverse event, rapid discontinuation can be considered. Caregivers should be told not to suddenly discontinue VIGAFYDE therapy.

5.6 Anemia

Across U.S. controlled trials, there were mean decreases in hemoglobin of about 3% and 0% in vigabatrin and placebo-treated patients, respectively, and a mean decrease in hematocrit of about 1% in vigabatrin-treated patients compared to a mean gain of about 1% in patients treated with placebo.

In controlled and open-label epilepsy trials in adults and pediatric patients, 3 vigabatrin patients (0.06%, 3/4,855) discontinued for anemia and 2 vigabatrin patients experienced unexplained declines in hemoglobin to below 8 g/dL and/or hematocrit below 24%.

5.7 Somnolence and Fatigue

VIGAFYDE causes somnolence and fatigue.

Pooled data from three vigabatrin controlled trials in pediatric patients demonstrated that 6% (10/165) of vigabatrin patients experienced somnolence compared to 5% (5/104) of placebo patients. In those same studies, 10% (17/165) of vigabatrin patients experienced fatigue compared to 7% (7/104) of placebo patients. No vigabatrin patients discontinued from clinical trials due to somnolence or fatigue.

VIGAFYDE is indicated for treatment in patients 1 month to 2 years of age [see Indications and Usage (1)]. VIGAFYDE is not approved for use in adults. Pooled data from two vigabatrin controlled trials in adults demonstrated that 24% (54/222) of vigabatrin patients experienced somnolence compared to 10% (14/135) of placebo patients. In those same studies, 28% of vigabatrin patients experienced fatigue compared to 15% (20/135) of placebo patients. Almost 1% of vigabatrin patients discontinued from clinical trials for somnolence and almost 1% discontinued for fatigue.

5.8 Peripheral Neuropathy

VIGAFYDE is indicated for treatment in patients 1 month to 2 years of age [see Indications and Usage (1)]. VIGAFYDE is not approved for use in adults. Vigabatrin causes symptoms of peripheral neuropathy in adults. Pediatric clinical trials were not designed to assess symptoms of peripheral neuropathy, but observed incidence of symptoms based on pooled data from controlled pediatric studies appeared similar for pediatric patients on vigabatrin and placebo. In a pool of North American controlled and uncontrolled epilepsy studies, 4.2% (19/457) of vigabatrin patients developed signs and/or symptoms of peripheral neuropathy. In the subset of North American placebo-controlled epilepsy trials, 1.4% (4/280) of vigabatrin treated patients and no (0/188) placebo patients developed signs and/or symptoms of peripheral neuropathy. Initial manifestations of peripheral neuropathy in these trials included, in some combination, symptoms of numbness or tingling in the toes or feet, signs of reduced distal lower limb vibration or position sensation, or progressive loss of reflexes, starting at the ankles. Clinical studies in the development program were not designed to investigate peripheral neuropathy systematically and did not include nerve conduction studies, quantitative sensory testing, or skin or nerve biopsy. There is insufficient evidence to determine if development of these signs and symptoms was related to duration of vigabatrin treatment, cumulative dose, or if the findings of peripheral neuropathy were completely reversible upon discontinuation of vigabatrin.

5.9 Weight Gain

VIGAFYDE causes weight gain in pediatric patients.

Data pooled from randomized controlled trials in pediatric patients with a different indication found that 47% (77/163) of vigabatrin patients versus 19% (19/102) of placebo patients gained ≥7% of baseline body weight.

In all epilepsy trials, 0.6% (31/4,855) of VIGAFYDE patients discontinued for weight gain. The long-term effects of vigabatrin related weight gain are not known. Weight gain was not related to the occurrence of edema.

5.10 Edema

VIGAFYDE is approved for use in patients 1 month to 2 years of age [see Indications and Usage (1)]. VIGAFYDE is not approved for use in adults. Vigabatrin causes edema in adults. Pediatric clinical trials were not designed to assess edema, but observed incidence of edema-based pooled data from controlled pediatric studies appeared similar for pediatric patients on vigabatrin and placebo.

Pooled data from controlled trials demonstrated increased risk among patients treated with vigabatrin powder for oral solution compared to placebo patients for peripheral edema (vigabatrin powder for oral solution 2%, placebo 1%), and edema (vigabatrin powder for oral solution 1%, placebo 0%). In these studies, one patient treated with vigabatrin powder for oral solution and no placebo patients discontinued for an edema related adverse event. In adults, there was no apparent association between edema and cardiovascular adverse events such as hypertension or congestive heart failure. Edema was not associated with laboratory changes suggestive of deterioration in renal or hepatic function.

5.11 Suicidal Behavior and Ideation with Unapproved Use in Adolescents and Adults

VIGAFYDE is approved for use in patients 1 month to 2 years of age [see Indications and Usage (1)]. VIGAFYDE is not approved for use in adolescents or adults. Antiepileptic drugs (AEDs) increase the risk of suicidal thoughts or behavior in adolescents and adults. Patients treated with any AED for any indication should be monitored for the emergence or worsening of depression, suicidal thoughts or behavior, and/or any unusual changes in mood or behavior.

Pooled analyses of 199 placebo-controlled clinical trials (mono- and adjunctive therapy) of 11 different AEDs showed that adult patients randomized to one of the AEDs had approximately twice the risk (adjusted relative risk 1.8, 95% confidence interval [CI]: 1.2, 2.7) of suicidal thinking or behavior compared to adult patients randomized to placebo. In these trials, which had a median treatment duration of 12 weeks, the estimated incidence rate of suicidal behavior or ideation among 27,863 AED-treated adult patients was 0.43%, compared to 0.24% among 16,029 placebo-treated adult patients, representing an increase of approximately one case of suicidal thinking or behavior for every 530 adult patients treated. There were four suicides in drug-treated adult patients in the trials and none in placebo-treated adult patients, but the number was too small to allow any conclusion about AED effect on suicide.

The increased risk of suicidal thoughts or behavior in adults with AEDs was observed as early as one week after starting AED treatment and persisted for the duration of treatment assessed. Because most trials included in the analysis did not extend beyond 24 weeks, the risk of suicidal thoughts or behavior beyond 24 weeks could not be assessed. The risk of suicidal thoughts or behavior was generally consistent among drugs in the data analyzed. The finding of increased risk with AEDs of varying mechanisms of action and across a range of indications suggests that the risk applies to all AEDs used for any indication.

6 ADVERSE REACTIONS

The following serious and otherwise important adverse reactions are described elsewhere in labeling:

- Permanent Vision Loss [see BOXED WARNING and Warnings and Precautions (5.1)]
- Magnetic Resonance Imaging (MRI) Abnormalities in Infants [see Warnings and Precautions (5.3)]
- Neurotoxicity [see Warnings and Precautions (5.4)]
- Withdrawal of Antiepileptic Drugs (AEDs) [see Warnings and Precautions (5.5)]
- Anemia [see Warnings and Precautions (5.6)]
- Somnolence and Fatigue [see Warnings and Precautions (5.7)]
- Peripheral Neuropathy [see Warnings and Precautions (5.8)]
- Weight Gain [see Warnings and Precautions (5.9)]
- Edema [see Warnings and Precautions (5.10)]
- Suicidal Behavior and Ideation with Unapproved use in Adolescents and Adults [see Warnings and Precautions (5.11)]

6.1 Clinical Trials Experience

Because clinical trials are conducted under widely varying conditions, adverse reaction rates observed in the clinical trials of a drug cannot be directly compared to rates in the clinical trials of another drug and may not reflect the rates observed in practice.

Infantile Spasms

In a randomized, placebo-controlled study in patients with infantile spasms (IS) with a 5 day double-blind treatment phase (n=40), the adverse reactions that occurred in ≥5% of patients receiving vigabatrin and that occurred more frequently than in placebo patients were somnolence (vigabatrin 45%, placebo 30%), bronchitis (vigabatrin 30%, placebo 15%), ear infection (vigabatrin 10%, placebo 5%), and acute otitis media (vigabatrin 10%, placebo 0%).

In patients with IS, the adverse reactions most commonly associated with vigabatrin treatment discontinuation in ≥1% of patients were infections, status epilepticus, developmental coordination disorder, dystonia, hypotonia, hypertonia, weight gain, and insomnia.

In a dose response study of low-dose (18 to 36 mg/kg/day, which is below the recommended starting dose for IS of 50 mg/kg/day) versus high-dose (100 to 148 mg/kg/day) vigabatrin, no clear correlation between dose and incidence of adverse reactions was observed. The adverse reactions (≥5% in either dose group) are summarized in Table 2.

Table 2. Adverse Reactions in a Placebo-Controlled Trial in Patients with Infantile Spasms
Body System Adverse Reaction | Vigabatrin Low Dose [N=114] % | Vigabatrin High Dose [N=108] %
Eye Disorders (other than field or acuity changes)
Strabismus | 5 | 5
Conjunctivitis | 5 | 2
Gastrointestinal Disorders
Vomiting | 14 | 20
Constipation | 14 | 12
Diarrhea | 13 | 12
General Disorders
Fever | 29 | 19
Infections
Upper respiratory tract infection | 51 | 46
Otitis media | 44 | 30
Viral infection | 20 | 19
Pneumonia | 13 | 11
Candidiasis | 8 | 3
Ear infection | 7 | 14
Gastroenteritis viral | 6 | 5
Sinusitis | 5 | 9
Urinary tract infection | 5 | 6
Influenza | 5 | 3
Croup infectious | 5 | 1
Metabolism & Nutrition Disorders
Decreased appetite | 9 | 7
Nervous System Disorders
Sedation | 19 | 17
Somnolence | 17 | 19
Status epilepticus | 6 | 4
Lethargy | 5 | 7
Convulsion | 4 | 7
Hypotonia | 4 | 6
Psychiatric Disorders
Irritability | 16 | 23
Insomnia | 10 | 12
Respiratory Disorders
Nasal congestion | 13 | 4
Cough | 3 | 8
Skin and Subcutaneous Tissue Disorders
Rash | 8 | 11

6.2 Postmarketing Experience

The following adverse reactions have been identified during postapproval use of vigabatrin. Because these reactions are reported voluntarily from a population of uncertain size, it is not always possible to reliably estimate their frequency or establish a causal relationship to drug exposure.

Ear Disorders: Deafness

Endocrine Disorders: Delayed puberty

Gastrointestinal Disorders: Gastrointestinal hemorrhage, esophagitis

General Disorders: Developmental delay, facial edema, malignant hyperthermia, multi-organ failure

Hepatobiliary Disorders: Cholestasis

Nervous System Disorders: Dystonia, encephalopathy, hypertonia, hypotonia, muscle spasticity, myoclonus, optic neuritis, dyskinesia

Psychiatric Disorders: Acute psychosis, apathy, delirium, hypomania, neonatal agitation, psychotic disorder

Respiratory Disorders: Laryngeal edema, pulmonary embolism, respiratory failure, stridor

Skin and Subcutaneous Tissue Disorders: Angioedema, maculo-papular rash, pruritus, Stevens-Johnson syndrome (SJS), toxic epidermal necrolysis (TEN), alopecia

7 DRUG INTERACTIONS

7.1 Antiepileptic Drugs

Phenytoin

Although phenytoin dose adjustments are not routinely required, dose adjustment of phenytoin should be considered if clinically indicated, since VIGAFYDE may cause a moderate reduction in total phenytoin plasma levels [see Clinical Pharmacology (12.3)].

Clonazepam

VIGAFYDE may moderately increase the Cmax of clonazepam resulting in an increase of clonazepam-associated adverse reactions [see Clinical Pharmacology (12.3)].

7.2 Drug-Laboratory Test Interactions

VIGAFYDE decreases alanine transaminase (ALT) and aspartate transaminase (AST) plasma activity in up to 90% of patients. In some patients, these enzymes become undetectable. The suppression of ALT and AST activity by vigabatrin may preclude the use of these markers, especially ALT, to detect early hepatic injury.

VIGAFYDE may increase the amount of amino acids in the urine, possibly leading to a false positive test for certain rare genetic metabolic diseases (e.g., alpha aminoadipic aciduria).

8 USE IN SPECIFIC POPULATIONS

8.1 Pregnancy

VIGAFYDE is indicated for treatment in patients 1 month to 2 years of age [see Indications and Usage (1)]. VIGAFYDE is not approved for use in adolescents and adults.

Pregnancy Exposure Registry
There is a pregnancy exposure registry that monitors pregnancy outcomes in women exposed to AEDs, including VIGAFYDE, during pregnancy. Encourage women who are taking VIGAFYDE during pregnancy to enroll in the North American Antiepileptic Drug (NAAED) Pregnancy Registry. This can be done by calling the toll-free number 1-888-233-2334 or visiting the website, http://www.aedpregnancyregistry.org/. This must be done by the patient herself.

Risk Summary
There are no adequate data on the developmental risk associated with the use of VIGAFYDE in pregnant women. Limited available data from case reports and cohort studies pertaining to vigabatrin use in pregnant women have not established a drug-associated risk of major birth defects, miscarriage, or adverse maternal or fetal outcomes. However, based on animal data, VIGAFYDE use in pregnant women may result in fetal harm.

When administered to pregnant animals, vigabatrin produced developmental toxicity, including an increase in fetal malformations and offspring neurobehavioral and neurohistopathological effects, at clinically relevant doses. In addition, developmental neurotoxicity was observed in rats treated with vigabatrin during a period of postnatal development corresponding to the third trimester of human pregnancy (see Data).

In the U.S. general population, the estimated background risk of major birth defects and miscarriage in clinically recognized pregnancies is 2 to 4% and 15 to 20%, respectively. The background risk of major birth defects and miscarriage for the indicated population is unknown.

Data

Animal Data

Administration of vigabatrin (oral doses of 50 to 200 mg/kg/day) to pregnant rabbits throughout the period of organogenesis was associated with an increased incidence of malformations (cleft palate) and embryofetal death; these findings were observed in two separate studies. The no-effect dose for adverse effects on embryofetal development in rabbits (100 mg/kg/day) is approximately 1/2 the maximum recommended human dose (MRHD) of 3 g/day on a body surface area (mg/m^2) basis. In rats, oral administration of vigabatrin (50, 100, or 150 mg/kg/day) throughout organogenesis resulted in decreased fetal body weights and increased incidences of fetal anatomic variations. The no-effect dose for adverse effects on embryo-fetal development in rats (50 mg/kg/day) is approximately 1/5 the MRHD on a mg/m^2 basis. Oral administration of vigabatrin (50, 100, 150 mg/kg/day) to rats from the latter part of pregnancy through weaning produced long-term neurohistopathological (hippocampal vacuolation) and neurobehavioral (convulsions) abnormalities in the offspring. A no-effect dose for developmental neurotoxicity in rats was not established; the low-effect dose (50 mg/kg/day) is approximately 1/5 the MRHD on a mg/m^2 basis.

In a published study, vigabatrin (300 or 450 mg/kg) was administered by intraperitoneal injection to a mutant mouse strain on a single day during organogenesis (day 7, 8, 9, 10, 11, or 12). An increase in fetal malformations (including cleft palate) was observed at both doses.

Oral administration of vigabatrin (5, 15, or 50 mg/kg/day) to young rats during the neonatal and juvenile periods of development (postnatal days 4 to 65) produced neurobehavioral (convulsions, neuromotor impairment, learning deficits) and neurohistopathological (brain vacuolation, decreased myelination, and retinal dysplasia) abnormalities in treated animals. The early postnatal period in rats is generally thought to correspond to late pregnancy in humans in terms of brain development. The no-effect dose for developmental neurotoxicity in juvenile rats (5 mg/kg/day) was associated with plasma vigabatrin exposures (AUC) less than 1/30 of those measured in pediatric patients receiving an oral dose of 50 mg/kg.

8.2 Lactation

VIGAFYDE is indicated for treatment in patients 1 month to 2 years of age [see Indications and Usage (1)]. VIGAFYDE is not approved for use in adolescents and adults.

Risk Summary
Vigabatrin is excreted in human milk. The effects of vigabatrin on the breastfed infant and on milk production are unknown. Because of the potential for serious adverse reactions from vigabatrin in nursing infants, breastfeeding is not recommended. If exposing a breastfed infant to VIGAFYDE, observe for any potential adverse effects [see Warnings and Precautions (5.1, 5.3, 5.4, 5.8)].

8.4 Pediatric Use

The safety and effectiveness of vigabatrin as monotherapy for pediatric patients with infantile spasms (1 month to 2 years of age) have been established [see Dosage and Administration (2.2) and Clinical Studies (14.1)].

Safety and effectiveness as a monotherapy for the treatment of infantile spasms in pediatric patients below the age of 1 month have not been established.

Duration of therapy for infantile spasms was evaluated in a post hoc analysis of a Canadian Pediatric Epilepsy Network (CPEN) study of developmental outcomes in infantile spasms patients. This analysis suggests that a total duration of 6 months of vigabatrin therapy is adequate for the treatment of infantile spasms. However, prescribers must use their clinical judgment as to the most appropriate duration of use [see Clinical Studies (14.1)].

Abnormal MRI signal changes and Intramyelinic Edema (IME) in infants and young children being treated with vigabatrin have been observed [see Warnings and Precautions (5.3, 5.4)].

Juvenile Animal Toxicity Data

Oral administration of vigabatrin (5, 15, or 50 mg/kg/day) to young rats during the neonatal and juvenile periods of development (postnatal days 4 to 65) produced neurobehavioral (convulsions, neuromotor impairment, learning deficits) and neurohistopathological (brain gray matter vacuolation, decreased myelination, and retinal dysplasia) abnormalities. The no-effect dose for developmental neurotoxicity in juvenile rats (the lowest dose tested) was associated with plasma vigabatrin exposures (AUC) substantially less than those measured in pediatric patients at recommended doses. In dogs, oral administration of vigabatrin (30 or 100 mg/kg/day) during selected periods of juvenile development (postnatal days 22 to 112) produced neurohistopathological abnormalities (brain gray matter vacuolation). Neurobehavioral effects of vigabatrin were not assessed in the juvenile dog. A no-effect dose for neurohistopathology was not established in juvenile dogs; the lowest effect dose (30 mg/kg/day) was associated with plasma vigabatrin exposures lower than those measured in pediatric patients at recommended doses [see Warnings and Precautions (5.4)].

8.5 Geriatric Use

VIGAFYDE is indicated for treatment in patients 1 month to 2 years of age [see Indications and Usage (1)]. VIGAFYDE is not approved for use in adults.

Clinical studies of vigabatrin did not include sufficient numbers of patients aged 65 and over to determine whether they responded differently from younger patients.

Vigabatrin is known to be substantially excreted by the kidney, and the risk of toxic reactions to this drug may be greater in patients with impaired renal function. Because elderly patients are more likely to have decreased renal function, care should be taken in dose selection, and it may be useful to monitor renal function.

Oral administration of a single dose of 1.5 g of vigabatrin to elderly (≥65 years) patients with reduced creatinine clearance (<50 mL/min) was associated with moderate to severe sedation and confusion in 4 of 5 patients, lasting up to 5 days. The renal clearance of vigabatrin was 36% lower in healthy elderly subjects (≥65 years) than in young healthy males. If used in elderly patients, adjustment of dose or frequency of administration should be considered.

Other reported clinical experience has not identified differences in responses between the elderly and younger patients.

8.6 Renal Impairment

Information about how to adjust the dose in infants with renal impairment is unavailable.

10 OVERDOSAGE

10.1 Signs, Symptoms, and Laboratory Findings of Overdosage

Confirmed and/or suspected vigabatrin overdoses have been reported during clinical trials and in post marketing surveillance. No vigabatrin overdoses resulted in death. When reported, the vigabatrin dose ingested ranged from 3 g to 90 g, but most were between 7.5 g and 30 g. Nearly half the cases involved multiple drug ingestions including carbamazepine, barbiturates, benzodiazepines, lamotrigine, valproic acid, acetaminophen, and/or chlorpheniramine.

Coma, unconsciousness, and/or drowsiness were described in the majority of cases of vigabatrin overdose. Other less commonly reported symptoms included vertigo, psychosis, apnea or respiratory depression, bradycardia, agitation, irritability, confusion, headache, hypotension, abnormal behavior, increased seizure activity, status epilepticus, and speech disorder. These symptoms resolved with supportive care.

10.2 Management of Overdosage

There is no specific antidote for VIGAFYDE overdose. Standard measures to remove unabsorbed drug should be used, including elimination by emesis or gastric lavage. Supportive measures should be employed, including monitoring of vital signs and observation of the clinical status of the patient.

In an in vitro study, activated charcoal did not significantly adsorb vigabatrin.

The effectiveness of hemodialysis in the treatment of VIGAFYDE overdose is unknown. In isolated case reports in renal failure patients receiving therapeutic doses of vigabatrin, hemodialysis reduced vigabatrin plasma concentrations by 40% to 60%.

11 DESCRIPTION

VIGAFYDE (vigabatrin) oral solution is an antiepileptic drug.

The chemical name of vigabatrin is (±) 4-amino-5-hexenoic acid, a racemic mixture of R and S isomers. The molecular formula is C6H11NO2 and the molecular weight is 129.16. It has the following structural formula:

Vigabatrin is a white to off-white powder which is freely soluble in water, slightly soluble in methyl alcohol, very slightly soluble in ethyl alcohol and chloroform, and insoluble in toluene and hexane. The pH of a 1% aqueous solution is about 6.9. The n-octanol/water partition coefficient of vigabatrin is about 0.011 (log P=-1.96) at physiologic pH. Vigabatrin melts with decomposition in a 3-degree range within the temperature interval of 171ºC to 176ºC. The dissociation constants (pKa) of vigabatrin are 4 and 9.7 at room temperature (25ºC).

Each mL of VIGAFYDE contains 100 mg of vigabatrin. The inactive ingredients are methylparaben; peppermint flavor; propylparaben; purified water; and sucralose.

12 CLINICAL PHARMACOLOGY

12.1 Mechanism of Action

The precise mechanism of vigabatrin’s anti-seizure effect is unknown, but it is believed to be the result of its action as an irreversible inhibitor of γ-aminobutyric acid transaminase (GABA-T), the enzyme responsible for the metabolism of the inhibitory neurotransmitter GABA. This action results in increased levels of GABA in the central nervous system.

No direct correlation between plasma concentration and efficacy has been established. The duration of drug effect is presumed to be dependent on the rate of enzyme re-synthesis rather than on the rate of elimination of the drug from the systemic circulation.

12.2 Pharmacodynamics

Effects on Electrocardiogram

There is no indication of a QT/QTc prolonging effect of vigabatrin in single doses up to 6.0 g. In a randomized, placebo-controlled, crossover study, 58 healthy subjects were administered a single oral dose of vigabatrin (3 g and 6 g) and placebo. Peak concentrations for 6.0 g vigabatrin were approximately 2-fold higher than the peak concentrations following the 3.0 g single oral dose.

12.3 Pharmacokinetics

VIGAFYDE is indicated for treatment in patients 1 month to 2 years of age [see Indications and Usage (1)]. VIGAFYDE is not approved for use in adults.

Vigabatrin displayed linear pharmacokinetics after administration of single doses ranging from 0.5 g to 4 g, and after administration of repeated doses of 0.5 g and 2.0 g twice daily. The following PK information (Tmax, half-life, and clearance) of vigabatrin was obtained from stand-alone PK studies and population PK analyses.

Absorption

Following oral administration, vigabatrin is essentially completely absorbed. The time to maximum concentration (Tmax) is approximately 2.5 hours for infants (5 months to 2 years of age). There was little accumulation with multiple dosing in adult and pediatric patients. A food effect study involving administration of vigabatrin to healthy volunteers under fasting and fed conditions indicated that the Cmax was decreased by 33%, Tmax was increased to 2 hours, and AUC was unchanged under fed conditions.

Distribution

Vigabatrin does not bind to plasma proteins. Vigabatrin is widely distributed throughout the body; mean steady-state volume of distribution is 1.1 L/kg (CV = 20%).

Metabolism and Elimination

Vigabatrin is not significantly metabolized; it is eliminated primarily through renal excretion. The terminal half-life of vigabatrin is about 5.7 hours for infants (5 months to 2 years of age). Following administration of [14]C-vigabatrin to healthy male volunteers, about 95% of total radioactivity was recovered in the urine over 72 hours with the parent drug representing about 80% of this. Vigabatrin induces CYP2C9 but does not induce other hepatic cytochrome P450 enzyme systems.

Specific Populations

Pediatric

The clearance of vigabatrin is 2.4 L/hr for infants (5 months to 2 years of age).

Gender

No gender differences were observed for the pharmacokinetic parameters of vigabatrin in patients.

Race

No specific study was conducted to investigate the effects of race on vigabatrin pharmacokinetics. A cross study comparison between 23 Caucasian and 7 Japanese patients who received 1, 2, and 4 g of vigabatrin indicated that the AUC, Cmax, and half-life were similar for the two populations. However, the mean renal clearance of Caucasians (5.2 L/hr) was about 25% higher than the Japanese (4.0 L/hr). Inter-subject variability in renal clearance was 20% in Caucasians and was 30% in Japanese.

Renal Impairment

Mean AUC increased by 30% and the terminal half-life increased by 55% (8.1 hr vs 12.5 hr) in adult patients with mild renal impairment (CLcr from >50 to 80 mL/min) in comparison to normal subjects.

Mean AUC increased by two-fold and the terminal half-life increased by two-fold in adult patients with moderate renal impairment (CLcr from >30 to 50 mL/min) in comparison to normal subjects.

Mean AUC increased by 4.5-fold and the terminal half-life increased by 3.5-fold in adult patients with severe renal impairment (CLcr from >10 to 30 mL/min) in comparison to normal subjects.

The effect of dialysis on VIGAFYDE clearance has not been adequately studied.

Infants with Renal Impairment

The effect of renal impairment on the pharmacokinetics of VIGAFYDE in infants is unknown.

Hepatic Impairment

Vigabatrin is not significantly metabolized. The pharmacokinetics of vigabatrin in patients with impaired liver function has not been studied.

Drug Interactions

Phenytoin

A 16% to 20% average reduction in total phenytoin plasma levels was reported in adult controlled clinical studies. In vitro drug metabolism studies indicate that decreased phenytoin concentrations upon addition of vigabatrin therapy are likely to be the result of induction of cytochrome P450 2C enzymes in some patients. Although phenytoin dose adjustments are not routinely required, dose adjustment of phenytoin should be considered if clinically indicated [see Drug Interactions (7.1)].

Clonazepam

In a study of 12 healthy adult volunteers, clonazepam (0.5 mg) co-administration had no effect on vigabatrin (1.5 g twice daily) concentrations. Vigabatrin increases the mean Cmax of clonazepam by 30% and decreases the mean Tmax by 45% [see Drug Interactions (7.1)].

Other AEDs

When co-administered with vigabatrin, phenobarbital concentration (from phenobarbital or primidone) was reduced by an average of 8% to 16%, and sodium valproate plasma concentrations were reduced by an average of 8%. These reductions did not appear to be clinically relevant. Based on population pharmacokinetics, carbamazepine, clorazepate, primidone, and sodium valproate appear to have no effect on plasma concentrations of vigabatrin [see Drug Interactions (7.1)].

Alcohol

Co-administration of ethanol (0.6 g/kg) with vigabatrin (1.5 g twice daily) indicated that neither drug influences the pharmacokinetics of the other.

13 NONCLINICAL TOXICOLOGY

13.1 Carcinogenesis, Mutagenesis, Impairment of Fertility

Carcinogenesis

Vigabatrin showed no carcinogenic potential in mouse or rat when given in the diet at doses up to 150 mg/kg/day for 18 months (mouse) or at doses up to 150 mg/kg/day for 2 years (rat). These doses are less than the maximum recommended human dose (MRHD) for infantile spasms (150 mg/kg/day).

Mutagenesis

Vigabatrin was negative in in vitro (Ames, CHO/HGPRT mammalian cell forward gene mutation, chromosomal aberration in rat lymphocytes) and in in vivo (mouse bone marrow micronucleus) assays.

Impairment of Fertility

No adverse effects on male or female fertility were observed in rats at oral doses up to 150 mg/kg/day.

14 CLINICAL STUDIES

The efficacy of VIGAFYDE is based upon a comparison of the compositional differences between vigabatrin for oral solution and VIGAFYDE oral solution.

The effectiveness of vigabatrin as monotherapy was established for infantile spasms in two multicenter controlled studies. Both studies were similar in terms of disease characteristics and prior treatments of patients and all enrolled infants had a confirmed diagnosis of infantile spasms.

Study 1

Study 1 (N=221) was a multicenter, randomized, low-dose high-dose, parallel-group, partially-blind (caregivers knew the actual dose but not whether their child was classified as low or high dose; EEG reader was blinded but investigators were not blinded) study to evaluate the safety and efficacy of vigabatrin in patients ˂2 years of age with new-onset infantile spasms. Patients with both symptomatic and cryptogenic etiologies were studied. The study was comprised of two phases. The first phase was a 14 to 21 day partially-blind phase in which patients were randomized to receive either low-dose (18 to 36 mg/kg/day) or high-dose (100 to 148 mg/kg/day) vigabatrin. Study drug was titrated over 7 days, followed by a constant dose for 7 days. If the patient became spasm-free on or before day 14, another 7 days of constant dose was administered. The primary efficacy endpoint of this study was the proportion of patients who were spasm-free for 7 consecutive days beginning within the first 14 days of vigabatrin therapy. Patients considered spasm-free were defined as those patients who remained free of spasms (evaluated according to caregiver response to direct questioning regarding spasm frequency) and who had no indication of spasms or hypsarrhythmia during 8 hours of closed-circuit television EEG recording (including at least one sleep-wake-sleep cycle) performed within 3 days of the seventh day of spasm freedom and interpreted by a blinded EEG reader. Seventeen patients in the high-dose group achieved spasm freedom compared with 8 patients in the low-dose group. This difference was statistically significant (p=0.0375). Primary efficacy results are shown in Table 3.

Table 3. Spasm Freedom by Primary Criteria (Study 1)
 | Vigabatrin Treatment Group
 | 18 to 36 mg/kg/day [N=114] n (%) | 100 to 148 mg/kg/day [N=107] n (%)
Patients who Achieved Spasm Freedom | 8 (7.0) | 17 (15.9)

p=0.0375

Note: Primary criteria were evaluated based on caregiver assessment plus CCTV EEG confirmation within 3 days of the seventh day of spasm freedom.

Study 2

Study 2 (N=40) was a multicenter, randomized, double-blind, placebo-controlled, parallel-group study consisting of a pre-treatment (baseline) period of 2 to 3 days, followed by a 5-day double-blind treatment phase during which patients were treated with vigabatrin (initial dose of 50 mg/kg/day with titration allowed to 150 mg/kg/day) or placebo. The primary efficacy endpoint in this study was the average percent change in daily spasm frequency, assessed during a pre-defined and consistent 2-hour window of evaluation, comparing baseline to the final 2 days of the 5-day double-blind treatment phase. No statistically significant differences were observed in the average frequency of spasms using the 2-hour evaluation window. However, a post-hoc alternative efficacy analysis, using a 24-hour clinical evaluation window found a statistically significant difference in the overall percentage of reductions in spasms between the vigabatrin group (68.9%) and the placebo group (17.0%) (p=0.030).

Duration of therapy for infantile spasms was evaluated in a post hoc analysis of a Canadian Pediatric Epilepsy Network (CPEN) study of developmental outcomes in infantile spasms patients. The 38/68 infants in the study who had responded to vigabatrin therapy (complete cessation of spasms and hypsarrhythmia) continued vigabatrin therapy for a total duration of 6 months therapy. The 38 infants who responded were then followed for an additional 18 months after discontinuation of vigabatrin to determine their clinical outcome. A post hoc analysis indicated no observed recurrence of infantile spasms in any of these 38 infants.

16 HOW SUPPLIED/STORAGE AND HANDLING

16.1 How Supplied

VIGAFYDE (vigabatrin) oral solution contains 100 mg/mL vigabatrin. It is a clear, colorless to light yellow, peppermint-flavored solution supplied in a white opaque high-density polyethylene (HDPE) 150 mL bottle in a carton (NDC 80789-003-15).

16.2 Storage and Handling

Store unopened bottles at room temperature between 20°C to 25°C (68°F to 77°F) with excursions permitted to 15°C to 30°C (59°F to 86°F) [See USP Controlled Room Temperature].

After opening, store bottle in a refrigerator or at room temperature between 2°C to 30°C (36°F to 86°F).

Discard the unused portion 90 days after first opening.

17 PATIENT COUNSELING INFORMATION

Advise caregivers to read the FDA-approved patient labeling (Medication Guide and Instructions for Use).

If a patient is switching from vigabatrin powder for oral solution, inform the caregiver that VIGAFYDE is more concentrated (100 mg/mL) compared to reconstituted solutions of vigabatrin powder for oral solution (50 mg/mL), and the volume of solution that should be given to their infant will be lower than previously prescribed.

Advise patients to stop using other products that contain vigabatrin.

Administration Instructions for VIGAFYDE Oral Solution

Physicians should confirm that caregiver(s) understand how to measure and administer the correct dose of VIGAFYDE oral solution to their infants. Advise caregivers to measure VIGAFYDE with the syringe provided by the pharmacy. A household teaspoon is not an accurate measuring device.

Instruct caregivers that VIGAFYDE should not be diluted prior to dosing.

Advise the caregiver that VIGAFYDE may be given orally or via gastrostomy (G) tube. Doses administered via gastrojejunal (GJ) tubes must be administered through the G-port. If VIGAFYDE will be administered via G-tube, provide instructions to the caregiver(s) as to how to flush the tube after administration.

Advise the caregiver to discard any remaining VIGAFYDE 90 days after first opening.

Permanent Vision Loss

Inform caregivers of the risk of permanent vision loss, particularly loss of peripheral vision, from VIGAFYDE, and the need for monitoring vision [see Warnings and Precautions (5.1)].

Monitoring of vision, including assessment of visual fields and visual acuity, is recommended at baseline (no later than 4 weeks after starting VIGAFYDE), at least every 3 months while on therapy, and about 3 to 6 months after discontinuation of therapy. In patients for whom vision testing is not possible, treatment may continue without recommended testing according to clinical judgment with appropriate caregiver counseling. Caregivers should be informed that if baseline or subsequent vision is not normal, VIGAFYDE should only be used if the benefits of VIGAFYDE treatment clearly outweigh the risks of additional vision loss.

Advise caregivers that vision testing may be insensitive and may not detect vision loss before it is severe. Also advise caregivers that if vision loss is documented, such loss is irreversible. Ensure that both of these points are understood by caregivers.

Caregivers should be informed that if changes in vision are suspected, they should notify their physician immediately.

VIGABATRIN REMS

VIGAFYDE is available only through a restricted program called the Vigabatrin REMS [see Warnings and Precautions (5.2)].

Inform caregivers of the following:

- Patients/caregivers must be enrolled in the program.
- VIGAFYDE is only available through pharmacies that are enrolled in the Vigabatrin REMS.

MRI Abnormalities in Infants

Inform caregiver(s) of the possibility that infants may develop an abnormal MRI signal of unknown clinical significance [see Warnings and Precautions (5.3)].

Withdrawal of VIGAFYDE Therapy

Instruct patients and caregivers not to suddenly discontinue VIGAFYDE therapy without consulting with their healthcare provider. As with all AEDs, withdrawal should normally be gradual [see Warnings and Precautions (5.5)].

Distributed by
UPSHER-SMITH LABORATORIES, LLC
Maple Grove, MN 55369

VIGAFYDE is a registered trademark of Pyros Pharmaceuticals, Inc.

PLEF0427-4-414

MEDICATION GUIDE
VIGAFYDE® (VIG-uh-fide)
(vigabatrin)

oral solution

What is the most important information I should know about VIGAFYDE?
VIGAFYDE can cause serious side effects, including:

- Permanent vision loss
- Magnetic resonance imaging (MRI) changes in babies with infantile spasms (IS)

1. Permanent vision loss:
VIGAFYDE can damage the vision of anyone who takes it. Some people can have severe loss particularly to their ability to see to the side when they look straight ahead (peripheral vision). With severe vision loss, your baby may only be able to see things straight in front of them (sometimes called “tunnel vision”). Your baby may also have blurry vision. If this happens, it will not get better.

- Vision loss in babies: Because of the risk of vision loss, VIGAFYDE is used in babies 1 month to 2 years of age with IS only when you and your baby's healthcare provider decide that the possible benefits of VIGAFYDE are more important than the risks.
- Parents or caregivers are not likely to recognize the symptoms of vision loss in babies until it is severe. Healthcare providers may not find vision loss in babies until it is severe.
- It is difficult to test vision in babies, but, to the extent possible, all babies should have their vision tested before starting VIGAFYDE or within 4 weeks after starting VIGAFYDE, and every 3 months after that until VIGAFYDE is stopped. Your baby should also have a vision test about 3 to 6 months after VIGAFYDE is stopped.
- Your baby may not be able to be tested. Your baby's healthcare provider will determine if your baby can be tested. If your baby cannot be tested, your baby's healthcare provider may continue prescribing VIGAFYDE, but your baby's healthcare provider will not be able to watch for any vision loss.

Tell your healthcare provider right away if you think that your baby is:

- not seeing as well as before taking VIGAFYDE.
- acting differently than normal.
- Even if your baby’s vision seems fine, it is important to get regular vision tests because damage can happen before your baby acts differently. Even these regular vision exams may not show the damage to your baby’s vision before it is severe and permanent.

- Because VIGAFYDE might cause permanent vision loss, it is available to healthcare providers and patients only under a special program called the Vigabatrin Risk Evaluation and Mitigation Strategy (REMS). VIGAFYDE can only be prescribed to people who are enrolled in this program. As part of the Vigabatrin REMS, it is recommended that your baby's healthcare provider test your baby's vision from time to time (periodically) while your baby is being treated with VIGAFYDE, and even after your baby stops treatment. Your baby's healthcare provider will explain the details of the Vigabatrin REMS to you. For more information, go to www.vigabatrinREMS.com or call 1-866-244-8175.

2. MRI changes in babies with IS:
Brain pictures taken by MRI show changes in some babies after they are given VIGAFYDE. It is not known if these changes are harmful.

What is VIGAFYDE?

- VIGAFYDE is a prescription medicine used to treat babies 1 month to 2 years of age who have infantile spasms (IS) if you and your baby’s healthcare provider decide the possible benefits of taking VIGAFYDE are more important than the possible risk of vision loss.

What should I tell my baby's healthcare provider before starting VIGAFYDE?

If you are a parent or caregiver whose baby has IS, before giving VIGAFYDE to your baby, tell your baby's healthcare provider about all of your baby’s medical conditions, including if your baby has or ever had:

- an allergic reaction to VIGAFYDE, such as hives, itching, or trouble breathing.
- any vision problems.
- any kidney problems.

Tell your baby's healthcare provider about all the medicines your baby takes, including prescription and over-the-counter medicines, vitamins, and herbal supplements. VIGAFYDE and other medicines may affect each other causing side effects.

How should my baby take VIGAFYDE?

- VIGAFYDE comes as an oral solution.
- Important: VIGAFYDE is more concentrated than vigabatrin solutions prepared from powder. The volume of VIGAFYDE solution prescribed by your baby’s healthcare provider may be less than the volume prescribed for other vigabatrin solutions prepared from powder. Always double check the volume (mL) that you are to give your baby when you get a new prescription filled.
- Your baby will receive VIGAFYDE from a specialty pharmacy.
- Give VIGAFYDE exactly as your baby's healthcare provider tells you to. VIGAFYDE is usually taken 2 times each day.
- VIGAFYDE may be given by mouth or given through a gastrostomy (G) tube. If VIGAFYDE is given through a gastrojejunal (GJ) tube, the G-port must be used.
  Give the medicine as directed by your baby’s healthcare provider, and flush the tube after administration with the amount of water recommended by your healthcare provider.
- VIGAFYDE may be taken with or without food.
- Before starting to give VIGAFYDE, talk to your baby’s healthcare provider about what you should do if a VIGAFYDE dose is missed.
- If your baby is taking VIGAFYDE for IS and the seizures do not improve within 2 to 4 weeks, your baby’s healthcare provider will stop prescribing VIGAFYDE.
- Do not stop taking VIGAFYDE suddenly. This can cause serious problems. Stopping VIGAFYDE or any seizure medicine suddenly can cause seizures that will not stop (status epilepticus) in people who are being treated for seizures. You should follow your baby's healthcare provider’s instructions on how to stop taking VIGAFYDE.
- Tell your baby’s healthcare provider right away about any increase in seizures when VIGAFYDE treatment is being stopped. Before your baby starts taking VIGAFYDE, speak to your baby’s healthcare provider about what to do if your baby misses a dose, vomits, spits up, or only takes part of the dose of VIGAFYDE.
- Do not stop taking VIGAFYDE without talking to your healthcare provider. If VIGAFYDE improves your baby’s seizures, you and your baby's healthcare provider should talk about whether the benefit of taking VIGAFYDE is more important than the risk of vision loss, and decide if your baby will continue to take VIGAFYDE.
- VIGAFYDE can be given to your baby at the same time as their meal.
- Measure the dose of VIGAFYDE using the syringe given to you by the pharmacy. A household teaspoon is not an accurate measuring device.
- Do not add water or other liquids to VIGAFYDE (do not dilute) when measuring the dose.
- See “Instructions for Use” for detailed information about how to give VIGAFYDE to your baby the right way.

What are the possible side effects of VIGAFYDE?
VIGAFYDE can cause serious side effects, including:

- See “What is the most important information I should know about VIGAFYDE?”
- VIGAFYDE may cause your baby to be sleepy. Sleepy babies may have a harder time suckling and feeding, or may be irritable.
- weight gain that happens without swelling.

The following serious side effects happen in adults who take vigabatrin (the active ingredient in VIGAFYDE). It is not known if these side effects also happen in babies who take VIGAFYDE.

- low red blood cell counts (anemia).
- nerve problems. Symptoms of a nerve problem can include numbness and tingling in toes or feet. It is not known if nerve problems will go away after treatment with VIGAFYDE is stopped.
- swelling.
- suicidal thoughts and ideation.

VIGAFYDE may make certain types of seizures worse. You should tell your baby’s healthcare provider right away if your baby’s seizures get worse. Tell your baby’s healthcare provider if you see any changes in your baby’s behavior.

The most common side effects of VIGAFYDE in babies include:

- sleepiness – VIGAFYDE may cause your baby to be sleepy. Sleepy babies may have a harder time suckling and feeding or may be irritable.
- ear infection
- swelling in the bronchial tubes (bronchitis)
- irritability

Tell your healthcare provider if your baby has any side effect that bothers them or does not go away. These are not all the possible side effects of VIGAFYDE.

Call your doctor for medical advice about side effects. You may report side effects to FDA at 1-800-FDA-1088.

How should I store VIGAFYDE?

- Store unopened bottles at room temperature between 68°F to 77°F (20°C to 25°C). After opening, store bottle in a refrigerator or at room temperature between 36°F to 86°F (2°C to 30°C).
- Throw away (discard) any opened bottle of VIGAFYDE 90 days after first opening, even if there is still medicine in the bottle.

Keep VIGAFYDE and all medicines out of the reach of children.

General information about the safe and effective use of VIGAFYDE.
Medicines are sometimes prescribed for purposes other than those listed in a Medication Guide. You can ask your pharmacist or healthcare provider for information about VIGAFYDE that is written for health professionals. Do not use VIGAFYDE for a condition for which it was not prescribed. Do not give VIGAFYDE to other people, even if they have the same symptoms. It may harm them.

What are the ingredients in VIGAFYDE?

Active Ingredient: vigabatrin

Inactive Ingredients: methylparaben, peppermint flavor, propylparaben, purified water, and sucralose

Distributed by
UPSHER-SMITH LABORATORIES, LLC
Maple Grove, MN 55369

VIGAFYDE is a registered trademark of Pyros Pharmaceuticals, Inc.

For more information, go to www.VIGAFYDE.com or call 1-888-650-3789.

This Medication Guide has been approved by the U.S. Food and Drug Administration

PLEF0427-4-414

Revised: 11/2025

PATIENT INFORMATION

INSTRUCTIONS FOR USE

VIGAFYDE® (VIG-uh-fide)

(vigabatrin) oral solution

Read this Instructions for Use before your baby starts taking VIGAFYDE and each time you get a refill. There may be new information. This information does not take the place of talking with your baby’s healthcare provider about your baby’s medical condition or treatment. Talk to your baby’s healthcare provider if you have any questions about the right dose of medicine to give your baby or how to measure it.

Powder Formulation Users
VIGAFYDE contains more vigabatrin, 100 mg per milliliter (mL) compared to other types (formulations) of vigabatrin prepared from powder, at 50 mg per mL.

If your baby is switching from vigabatrin prepared from powder to VIGAFYDE oral solution, your baby’s healthcare provider may have prescribed a smaller volume (mL) of medicine than before.

Important Note:

- VIGAFYDE is a concentrated solution compared to other vigabatrin types. Each mL of VIGAFYDE contains 100 mg of vigabatrin.

Each VIGAFYDE oral solution carton contains (see Figure A):

- 1 bottle of VIGAFYDE oral solution
- 1 Medication Guide/Instructions for Use leaflet (not pictured)

The pharmacy will provide (see Figure B) an:

- Oral Syringe
- Bottle Adapter

- Your baby's healthcare provider will tell you how many milliliters (mL) of VIGAFYDE you will need for each dose.
- VIGAFYDE may be given by mouth or given through a gastrostomy (G) tube. If VIGAFYDE is given through a gastrojejunal (GJ) tube, the G-port must be used. Give the medicine as directed by your baby’s healthcare provider and flush the tube after administration with the amount of water recommended by your healthcare provider.
- If giving VIGAFYDE by mouth, use the oral syringe provided by the pharmacy to measure and give the prescribed dose. Do not use a household teaspoon or tablespoon.
- Stop using other products that contain vigabatrin. Check with your healthcare provider.
- Check the label on the bottle and make sure the expiration date (EXP) has not passed. If the expiration date has passed, do not use VIGAFYDE. Contact your pharmacy or healthcare provider to get a new bottle of VIGAFYDE.

How to prepare the bottle for first time use of VIGAFYDE oral solution:

Step 1: If needed, separate the bottle adapter from the oral syringe (see Figure C).

Step 2: Remove the child-resistant-cap by pressing down on the cap and turning it counterclockwise (to the left) (see Figure D). Do not throw away the child-resistant cap.

Step 3: Completely remove the inner seal from the bottle and throw it away in the household trash. If needed, the tip of the syringe may be used to puncture the inner seal (see Figure E).

Inserting the bottle adapter into the VIGAFYDE bottle:

Step 4: Insert the bottle adapter. While holding the bottle firmly on a flat surface, push the ribbed end of the bottle adapter all the way into the neck of the bottle. Make sure that the bottle adapter is fully inserted (see Figure F). Do not remove the bottle adapter from the bottle after it is inserted.

Step 5: Put the child-resistant cap back on the bottle by turning it clockwise (to the right). Record the date of opening on the bottle’s label. VIGAFYDE may be used for up to 90 days after first opening (see Figure G).

How to prepare a dose of VIGAFYDE oral solution:

Step 6: Open the bottle of VIGAFYDE by pressing down on the cap and turning it counterclockwise (to the left) (See Figure D).

Step 7: Use the oral syringe provided by the pharmacy to draw up the total number of mLs of medicine that your baby’s healthcare provider tells you to give.

Push the plunger of the oral syringe all the way up towards the tip of the oral syringe to remove air in the oral syringe (see Figure H).

Step 8: Place the VIGAFYDE bottle on a flat surface. While keeping the bottle in an upright position, insert the tip of the oral syringe into the opening of the bottle adapter and push down gently (see Figure I).

Step 9: While holding the oral syringe firmly into the bottle, turn the bottle upside down. Slowly pull back the plunger of the oral syringe until the top of the plunger stopper lines up with the mL marking (dose markings) on the barrel of the oral syringe that matches the number of mLs of medicine your baby’s healthcare provider told you to give (see Figure J).

After the prescribed dose is withdrawn, hold the plunger in place to keep the plunger from moving.

How to remove large air bubbles and measure to the prescribed dose:

Step 10: With the oral syringe attached to the bottle, check for air bubbles. Tiny air bubbles are normal. If large air bubbles are present (see Figure K), slowly push up on the plunger until the bubbles are removed. Then slowly pull back on the plunger to measure the prescribed dose. The top of the plunger stopper must line up with the mL markings (dose markings) on the oral syringe for the prescribed dose.

Step 11: Continue to hold the plunger in place to keep the plunger from moving. Leave the oral syringe in the bottle adapter and turn the bottle to an upright position. Place the bottle onto a flat surface. Carefully remove the oral syringe from the bottle adapter by gently pulling straight up on the oral syringe while holding the plunger in place (See Figure L).

Check to make sure that the dose in the oral syringe is the prescribed dose. If the dose of VIGAFYDE is not the right dose, insert the oral syringe tip firmly into the bottle adapter while the bottle is in an upright position. Push the plunger all the way down so that VIGAFYDE flows back into the bottle and repeat Steps 9 through 11.

How to give a dose of VIGAFYDE oral solution:

Step 12:

- Giving the dose by mouth: Sit your baby upright when giving a dose of VIGAFYDE. Place the tip of the oral syringe into your baby’s mouth and point the oral syringe towards either cheek (see Figure M). Push on the plunger slowly, a small amount at a time, until all the medicine in the oral syringe is given.

- Giving the dose by gastrostomy (G) tube: If VIGAFYDE is given through a gastrojejunal (GJ) tube, the G-port must be used. Give the medicine as directed by your baby's healthcare provider. Then flush the tube after giving the medicine with the amount of water recommended by your baby's healthcare provider.

If the dose you are giving your baby is more medicine than will fit into the syringe provided by the pharmacy, repeat steps 8 to 12 until you give the total dose of medicine prescribed by your healthcare provider.

Step 13: Leave the bottle adapter in place. Put the child-resistant cap back on the bottle by turning it clockwise (to the right). See Figure N.

How to clean the oral syringe after use:

Step 14: Rinse the oral syringe with warm water. To clean the oral syringe, remove the plunger by gently pulling it straight out of the barrel of the oral syringe. The barrel and plunger can be rinsed with water, and allowed to air dry. After the oral syringe barrel and plunger are dry, put the plunger back into the oral syringe barrel and store the oral syringe with your medicine.

How should I store VIGAFYDE?

- Store unopened bottles at room temperature between 68°F to 77°F (20°C to 25°C). After opening, store bottle in a refrigerator or at room temperature between 36°F to 86°F (2°C to 30°C).
- Throw away (discard) any opened bottle of VIGAFYDE 90 days after first opening, even if there is still medicine in the bottle.
- Keep VIGAFYDE and all medicines out of the reach of children.

Distributed by

UPSHER-SMITH LABORATORIES, LLC
Maple Grove, MN 55369

VIGAFYDE is a registered trademark of Pyros Pharmaceuticals, Inc.

This Instructions for Use has been approved by the U.S. Food and Drug Administration.

PLEF0427-4-414

Revised: 11/2025

PRINCIPAL DISPLAY PANEL

NDC 80789-003-15
VIGAFYDE®
(vigabatrin) oral solution
100 mg/mL
150 mL carton
Rx Only